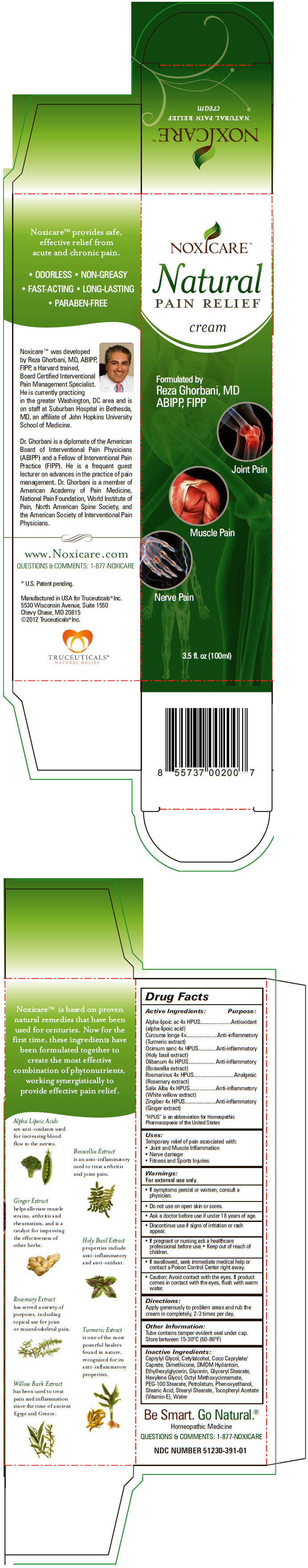 DRUG LABEL: NOXICARE
NDC: 51230-391 | Form: CREAM
Manufacturer: Truceuticals, LLC
Category: homeopathic | Type: HUMAN OTC DRUG LABEL
Date: 20121220

ACTIVE INGREDIENTS: .Alpha.-Lipoic Acid 4 [hp_X]/100 mL; Turmeric 4 [hp_X]/100 mL; Ocimum Tenuiflorum Top 4 [hp_X]/100 mL; Indian Frankincense 4 [hp_X]/100 mL; Rosemary 4 [hp_X]/100 mL; Salix Alba Bark 4 [hp_X]/100 mL; Ginger 4 [hp_X]/100 mL
INACTIVE INGREDIENTS: Caprylyl Glycol; Cetyl Alcohol; Coco-Caprylate/Caprate; Dimethicone; DMDM Hydantoin; Ethylhexylglycerin; Glycerin; Glyceryl Monostearate; Hexylene Glycol; Octinoxate; PEG-100 Stearate; Petrolatum; Phenoxyethanol; Stearic Acid; Stearyl Stearate; .Alpha.-Tocopherol; Water

NOXICARE™

Drug Facts

ACTIVE INGREDIENT

Active Ingredients: | PURPOSE
Alpha-lipoic ac 4x HPUS (alpha-lipoic acid) | Antioxidant
Curcuma longa 4x (Turmeric extract) | Anti-inflammatory
Ocimum sanc 4x HPUS (Holy basil extract) | Anti-inflammatory
Olibanum 4x HPUS (Boswellia extract) | Anti-inflammatory
Rosmarinus 4x HPUS (Rosemary extract) | Analgesic
Salix Alba 4x HPUS (White willow extract) | Anti-inflammatory
Zingiber 4x HPUS (Ginger extract) | Anti-inflammatory
"HPUS" is an abbreviation for Homeopathic Pharmacopoeia of the United States

Uses

Temporary relief of pain associated with:

- Joint and Muscle Inflammation
- Nerve damage
- Fitness and Sports Injuries

Warnings

For external use only.

ASK DOCTOR

- If symptoms persist or worsen, consult a physician.

- Do not use on open skin or sores.

- Ask a doctor before use if under 18 years of age.

STOP USE

- Discontinue use if signs of irritation or rash appear.

PREGNANCY OR BREAST FEEDING

- If pregnant or nursing ask a healthcare professional before use.

- Keep out of reach of children.
- If swallowed, seek immediate medical help or contact a Poison Control Center right away.

DO NOT USE

- Caution: Avoid contact with the eyes. If product comes in contact with the eyes, flush with warm water.

Directions

Apply generously to problem areas and rub the cream in completely, 2-3 times per day.

Other Information

Tube contains tamper-evident seal under cap. Store between 15-30°C (60-86°F)

Inactive Ingredients

Caprylyl Glycol, Cetylalcohol, Coco Caprylate/Caprate, Dimethicone, DMDM Hydantoin, Ethylhexylglycerin, Glycerin, Glyceryl Stearate, Hexylene Glycol, Octyl Methoxycinnamate, PEG-100 Stearate, Petrolatum, Phenoxyethanol, Stearic Acid, Stearyl Stearate, Tocopheryl Acetate (Vitamin-E), Water

QUESTIONS & COMMENTS

877-NOXICARE

Manufactured in USA for Truceuticals® Inc.
5530 Wisconsin Avenue, Suite 1550
Chevy Chase, MD 20815

PRINCIPAL DISPLAY PANEL - 100ml Tube Carton

NOXICARE™

Natural
PAIN RELIEF
cream

Formulated by
Reza Ghorbani, MD
ABIPP, FIPP

Joint Pain

Muscle Pain

Nerve Pain

3.5 fl. oz (100ml)